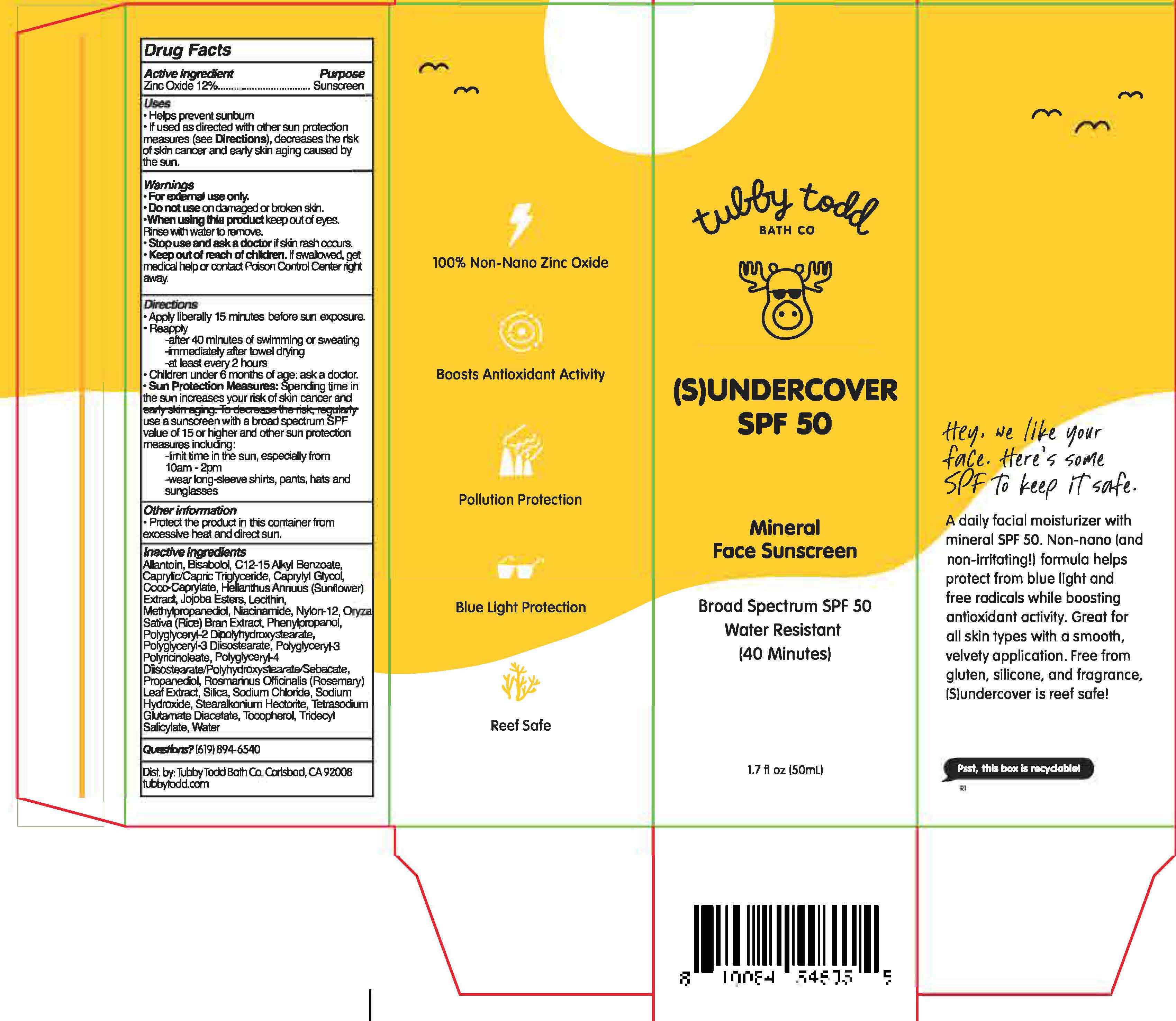 DRUG LABEL: (S)UNDERCOVER
NDC: 73088-106 | Form: LOTION
Manufacturer: TUBBY TODD
Category: otc | Type: HUMAN OTC DRUG LABEL
Date: 20241223

ACTIVE INGREDIENTS: ZINC OXIDE 12 g/100 mL
INACTIVE INGREDIENTS: ALLANTOIN; HYDROLYZED JOJOBA ESTERS; SODIUM HYDROXIDE; TOCOPHEROL; WATER; MEDIUM-CHAIN TRIGLYCERIDES; ALKYL (C12-15) BENZOATE; CAPRYLYL GLYCOL; COCO-CAPRYLATE; HELIANTHUS ANNUUS WHOLE; HYDROGENATED JOJOBA OIL/JOJOBA OIL, RANDOMIZED (IODINE VALUE 40-44); LECITHIN, SUNFLOWER; PHENYLPROPANOL; POLYGLYCERYL-2 DIPOLYHYDROXYSTEARATE; POLYGLYCERYL-4 DIISOSTEARATE/POLYHYDROXYSTEARATE/SEBACATE; PROPANEDIOL; ROSMARINUS OFFICINALIS WHOLE; SILICON DIOXIDE; SODIUM CHLORIDE; TETRASODIUM GLUTAMATE DIACETATE; NYLON-12; RICE BRAN; BISABOLOL; NIACINAMIDE; TRIDECYL SALICYLATE; POLYGLYCERYL-3 PENTARICINOLEATE; METHYLPROPANEDIOL; STEARALKONIUM HECTORITE; POLYGLYCERYL-3 DIISOSTEARATE

Tubby Todd - (S)UNDERCOVER SPF-50 (73088-106)

ACTIVE INGREDIENTS

Zinc Oxide 12%

PURPOSE

SUNSCREEN

USES

• Helps prevent sunburn.
• If used as directed with other sun protection measures (see Directions), decreases the risk of skin cancer and early skin aging caused by the sun.

WARNINGS

• For external use only.
• Do not use on damaged or broken skin.
• When using this product keep out of eyes. Rinse with water to remove.
• Stop use and ask a doctor if rash occurs.

Keep out of reach of children. If swallowed, get medical help or contact a Poison Control Center right away.

DIRECTIONS

- Apply generously 15 minutes before sun exposure and as needed.
- Reapply
- after 40 minutes of swimming or sweating
- immediately after towel drying
- at least every 2 hours
- Children under 6 months of age: ask a doctor.

- Sun Protection Measures: Spending time in the sun increases your risk of skin cancer and early skin aging. To decrease this risk, regularly use a sunscreen with a Broad Spectrum SPF value of 15 or higher and other sun protection measures including:
- limit time in the sun, especially from 10am-2pm
- wear long-sleeved shirts, pants, hats, and sunglasses.

OTHER INFORMATION

- PROTECT THE PRODUCT IN THIS CONTAINER FROM EXCESSIVE HEAT AND DIRECT SUN.

INACTIVE INGREDIENT

Allantoin, Bisabolol, C12-15 Alkyl Benzoate, Caprylic/Capric Triglyceride, Caprylyl Glycol, Coco-Caprylate, Helianthus Annuus (Sunflower) Extract, Jojoba Esters, Lecithin, Methylpropanediol, Niacinamide, Nylon-12, Orza Sativa (Rice) Bran Extract, Phenylpropanol, Polyglyceryl-2 Dipolyhydroxystearate, Polyglyceryl-3 Diisostearate, Polyglyceryl-3 Polyricinoleate, Polyglyceryl-4 Diisostearate/Polyhydroxystearate/Sebacate, Propanediol, Rosmarinus Officinalis (Rosemary) Leaf Extract, Silica, Sodium Chloride, Sodium Hydroxide, Stearalkonium Hectorite, Tetrasodium Glutamate Diacetate, Tocopherol, Tridecyl Salicylate, Water

QUESTIONS

(619) 894-6560